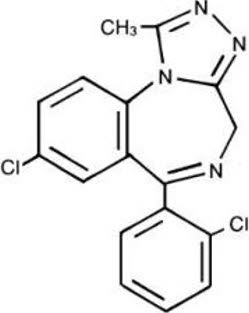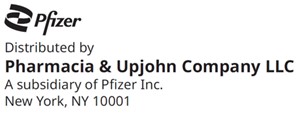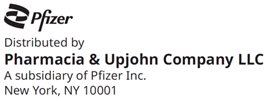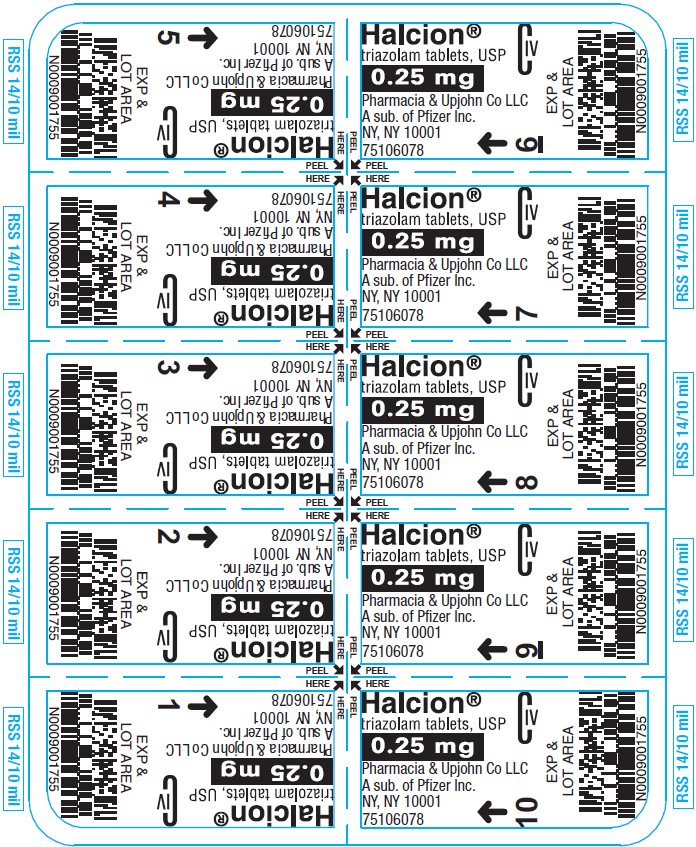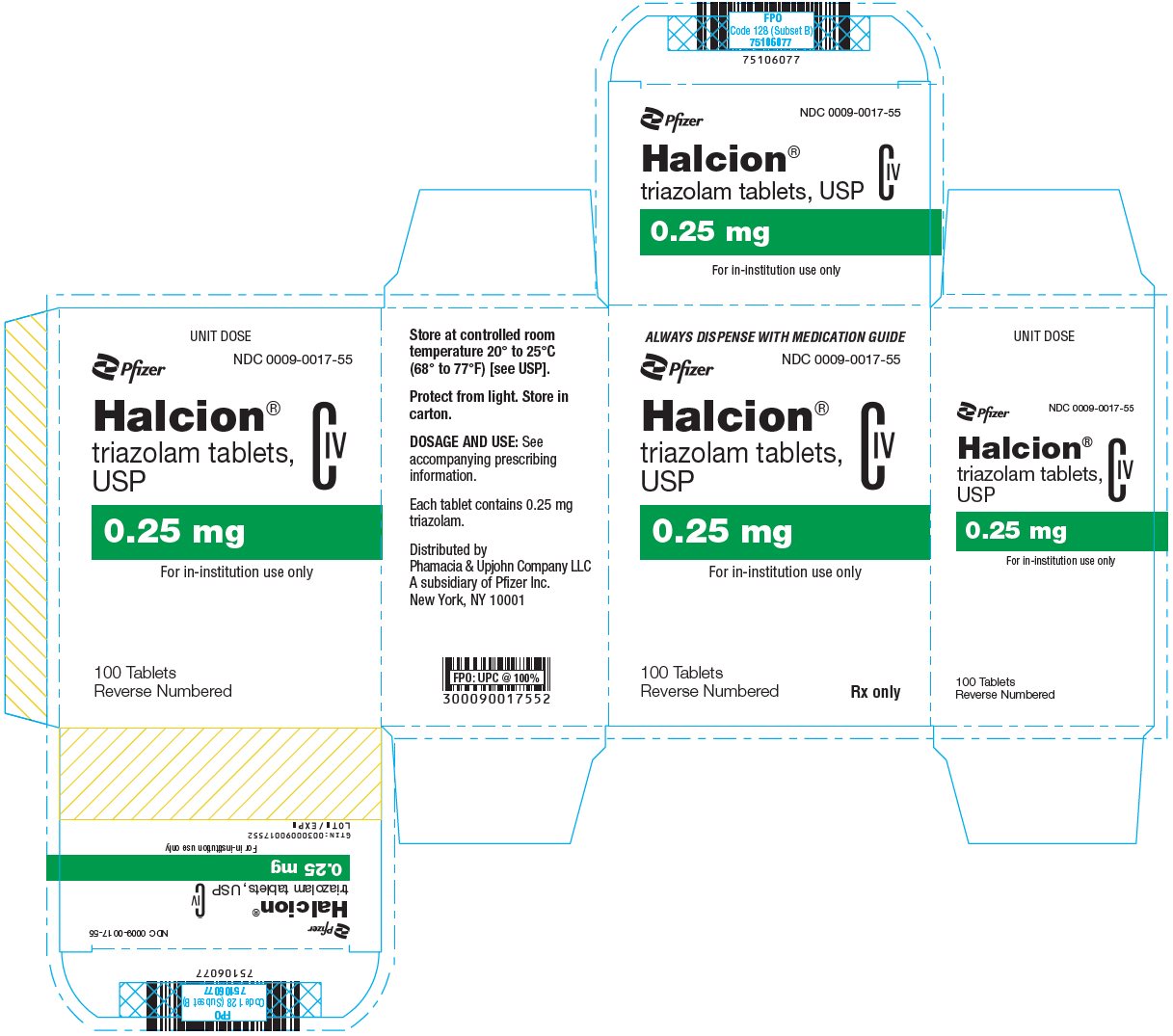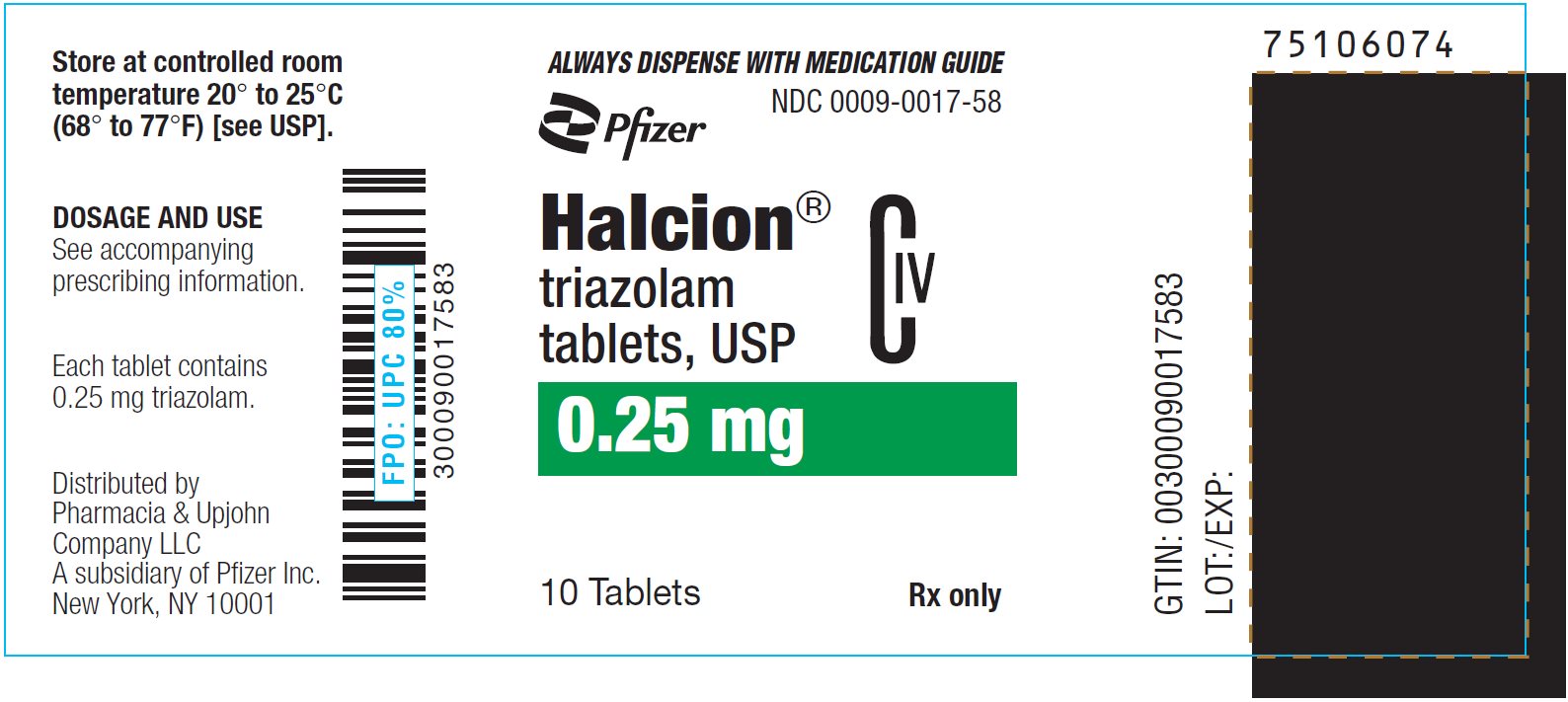 DRUG LABEL: Halcion
NDC: 0009-0017 | Form: TABLET
Manufacturer: Pharmacia & Upjohn Company LLC
Category: prescription | Type: HUMAN PRESCRIPTION DRUG LABEL
Date: 20260129
DEA Schedule: CIV

ACTIVE INGREDIENTS: TRIAZOLAM 0.25 mg/1 1
INACTIVE INGREDIENTS: POWDERED CELLULOSE; STARCH, CORN; DOCUSATE SODIUM; FD&C BLUE NO. 2; LACTOSE, UNSPECIFIED FORM; MAGNESIUM STEARATE; SILICON DIOXIDE; SODIUM BENZOATE

HIGHLIGHTS OF PRESCRIBING INFORMATION

These highlights do not include all the information needed to use HALCION safely and effectively. See full prescribing information for HALCION.
HALCION® (triazolam) tablets, for oral use, CIV
Initial U.S. Approval: 1982

WARNING: RISKS FROM CONCOMITANT USE WITH OPIOIDS; ABUSE, MISUSE, AND ADDICTION; and DEPENDENCE AND WITHDRAWAL REACTIONS

See full prescribing information for complete boxed warning.

- Concomitant use of benzodiazepines and opioids may result in profound sedation, respiratory depression, coma, and death. Reserve concomitant prescribing of these drugs in patients for whom alternative treatment options are inadequate. Limit dosages and durations to the minimum required. Follow patients for signs and symptoms of respiratory depression and sedation (5.1, 7.1).
- The use of benzodiazepines, including Halcion, exposes users to risks of abuse, misuse, and addiction, which can lead to overdose or death. Before prescribing Halcion and throughout treatment, assess each patient's risk for abuse, misuse, and addiction (5.2).
- Abrupt discontinuation or rapid dosage reduction of Halcion after continued use may precipitate acute withdrawal reactions, which can be life-threatening. To reduce the risk of withdrawal reactions, use a gradual taper to discontinue Halcion or reduce the dosage (2.3, 5.3).

1 INDICATIONS AND USAGE

Halcion is a benzodiazepine indicated for the short-term treatment of insomnia (generally 7 to 10 days) in adults. (1)

2 DOSAGE AND ADMINISTRATION

- Adults: Recommended dosage is 0.25 mg once daily before bedtime. Maximum recommended dosage is 0.5 mg once daily (2.1)
- Geriatric patients: Reduce starting dosage to 0.125 mg once daily. May increase to 0.25 mg if no response. Geriatric patients should not exceed 0.25 mg once daily (2.2, 8.5)
- Halcion should not be prescribed in quantities exceeding a 1-month supply (2.1)

3 DOSAGE FORMS AND STRENGTHS

Scored tablets: 0.25 mg (3)

4 CONTRAINDICATIONS

- Known hypersensitivity to Halcion or other benzodiazepines (4)
- Concomitant use with medications that significantly impair the oxidative metabolism mediated by cytochrome P450 3A (CYP 3A) including ketoconazole, itraconazole, nefazodone, and several human immunodeficiency virus (HIV) protease inhibitors (4, 5.8, 17)

5 WARNINGS AND PRECAUTIONS

- Persistent or Worsening Insomnia: Since sleep disturbances may be the presenting manifestation of a physical and/or psychiatric disorder, symptomatic treatment of insomnia should be initiated only after a careful evaluation of the patient. The failure of insomnia to remit after 7 to 10 days of treatment may indicate the presence of a primary psychiatric and/or medical illness that should be evaluated. (5.4)
- "Sleep-driving" and Other Complex Behaviors: Complex behaviors such as "sleep-driving" have been reported. The use of alcohol and other central nervous system (CNS) depressants with sedative-hypnotics appears to increase the risk, as well as doses exceeding the maximum recommended dose. (5.5)
- CNS Manifestations: An increase in daytime anxiety, abnormal thinking, and behavioral changes have been reported. Emergence of any new behavioral changes require careful and immediate evaluation. (5.6)
- Effects on Driving and Operating Heavy Machinery: Patients receiving triazolam should be cautioned against driving or operating heavy machinery, as well as avoiding concomitant use with alcohol and other CNS depressant drugs. (5.7)
- Patients with Depression: Caution should be exercised in patients with signs or symptoms of depression that could be intensified by hypnotic drugs. Prescribe the least number of tablets feasible to avoid intentional overdose. (5.9)
- Neonatal Sedation and Withdrawal Syndrome: Halcion use during pregnancy can result in neonatal sedation and/or neonatal withdrawal. (5.10, 8.1)

6 ADVERSE REACTIONS

Most common adverse reactions (incidence ≥4% and twice placebo) are drowsiness, dizziness, light-headedness, and coordination disorder/ataxia. (6.1)
To report SUSPECTED ADVERSE REACTIONS, contact Pfizer Inc. at 1-800-438-1985 or FDA at 1-800-FDA-1088 or www.fda.gov/medwatch.

7 DRUG INTERACTIONS

- Use with Opioids: Increase the risk of respiratory depression (7.1)
- Use with Other CNS Depressants: Produces additive CNS depressant effects (7.1)
- Use with CYP 3A4 Inhibitors: Increased risk of adverse reactions (4, 5.8, 7.1)

8 USE IN SPECIFIC POPULATIONS

Lactation: A lactating woman may pump and discard breast milk during treatment and for 28 hours after HALCION administration (8.2)

FULL PRESCRIBING INFORMATION

WARNING: RISKS FROM CONCOMITANT USE WITH OPIOIDS; ABUSE, MISUSE, AND ADDICTION; and DEPENDENCE AND WITHDRAWAL REACTIONS

- Concomitant use of benzodiazepines and opioids may result in profound sedation, respiratory depression, coma, and death. Reserve concomitant prescribing of these drugs in patients for whom alternative treatment options are inadequate. Limit dosages and durations to the minimum required. Follow patients for signs and symptoms of respiratory depression and sedation [see Warnings and Precautions (5.1), Drug Interactions (7.1)].
- The use of benzodiazepines, including Halcion, exposes users to risks of abuse, misuse, and addiction, which can lead to overdose or death. Abuse and misuse of benzodiazepines commonly involve concomitant use of other medications, alcohol, and/or illicit substances, which is associated with an increased frequency of serious adverse outcomes. Before prescribing Halcion and throughout treatment, assess each patient's risk for abuse, misuse, and addiction [see Warnings and Precautions (5.2)].
- The continued use of benzodiazepines, including Halcion, may lead to clinically significant physical dependence. The risks of dependence and withdrawal increase with longer treatment duration and higher daily dose. Abrupt discontinuation or rapid dosage reduction of Halcion after continued use may precipitate acute withdrawal reactions, which can be life-threatening. To reduce the risk of withdrawal reactions, use a gradual taper to discontinue Halcion or reduce the dosage [see Dosage and Administration (2.3), Warnings and Precautions (5.3)].

1 INDICATIONS AND USAGE

Halcion is indicated for the short-term treatment of insomnia (generally 7 to 10 days) in adults.

2 DOSAGE AND ADMINISTRATION

2.1 Dosing Information

The recommended dosage is 0.25 mg once daily before bedtime. A dosage of 0.125 mg once daily may be sufficient for some patients (e.g., patients with low body weight). A dosage of 0.5 mg should be used only for patients who do not respond adequately to a trial of a lower dose. The maximum recommended dosage is 0.5 mg once daily.

Use the lowest effective dose for the patient as there are significant dose related adverse reactions.

Use of Halcion for more than 3 weeks requires evaluation of the patient for a primary psychiatric or medical condition [see Warnings and Precautions (5.4, 5.6)].

Prescriptions for Halcion should be written for short-term use (7 to 10 days) and it should not be prescribed in quantities exceeding a 1-month supply.

2.2 Use in Geriatric Patients

In geriatric patients, the recommended dosage is 0.125 mg to 0.25 mg once daily. Initiate therapy at 0.125 mg once daily. The 0.25 mg dose should be used only for patients who do not respond to a trial of the lower dose. The maximum recommended dosage is 0.25 mg once daily. Elderly patients have an increased risk of dose related adverse reactions [see Use in Specific Populations (8.5)].

2.3 Discontinuation or Dosage Reduction of Halcion

To reduce the risk of withdrawal reactions, use a gradual taper to discontinue Halcion or reduce the dosage. If a patient develops withdrawal reactions, consider pausing the taper or increasing the dosage to the previous tapered dosage level. Subsequently decrease the dosage more slowly [see Warnings and Precautions (5.3), Drug Abuse and Dependence (9.3)].

3 DOSAGE FORMS AND STRENGTHS

Halcion is available as 0.25 mg tablets. The tablets are powder blue, elliptical, scored, and imprinted with HALCION 0.25.

4 CONTRAINDICATIONS

Halcion is contraindicated in:

- Patients with known hypersensitivity to triazolam, any of component of Halcion, or other benzodiazepines. Reactions consistent with angioedema (involving the tongue, glottis, or larynx), dyspnea, and throat closing have been reported and may be fatal.
- Concomitant administration of strong cytochrome P450 (CYP 3A) enzyme inhibitors (e.g., ketoconazole, itraconazole, nefazodone, lopinavir, ritonavir) [see Warnings and Precautions (5.8), Drug Interactions (7.1)].

5 WARNINGS AND PRECAUTIONS

5.1 Risks From Concomitant Use With Opioids

Concomitant use of benzodiazepines, including Halcion, and opioids may result in profound sedation, respiratory depression, coma, and death. Because of these risks, reserve concomitant prescribing of these drugs in patients for whom alternative treatment options are inadequate.

Observational studies have demonstrated that concomitant use of opioid analgesics and benzodiazepines increases the risk of drug-related mortality compared to use of opioids alone. If a decision is made to prescribe Halcion concomitantly with opioids, prescribe the lowest effective dosages and minimum durations of concomitant use, and follow patients closely for signs and symptoms of respiratory depression and sedation. In patients already receiving an opioid analgesic, prescribe a lower initial dose of Halcion than indicated in the absence of an opioid and titrate based on clinical response. If an opioid is initiated in a patient already taking Halcion, prescribe a lower initial dose of the opioid and titrate based upon clinical response.

Advise both patients and caregivers about the risks of respiratory depression and sedation when Halcion is used with opioids. Advise patients not to drive or operate heavy machinery until the effects of concomitant use with the opioid have been determined [see Drug Interactions (7.1)].

5.2 Abuse, Misuse, and Addiction

The use of benzodiazepines, including Halcion, exposes users to the risks of abuse, misuse, and addiction, which can lead to overdose or death. Abuse and misuse of benzodiazepines often (but not always) involve the use of doses greater than the maximum recommended dosage and commonly involve concomitant use of other medications, alcohol, and/or illicit substances, which is associated with an increased frequency of serious adverse outcomes, including respiratory depression, overdose, or death [see Drug Abuse and Dependence (9.2)].

Before prescribing Halcion and throughout treatment, assess each patient's risk for abuse, misuse, and addiction (e.g., using a standardized screening tool). Use of Halcion, particularly in patients at elevated risk, necessitates counseling about the risks and proper use of Halcion along with monitoring for signs and symptoms of abuse, misuse, and addiction. Prescribe the lowest effective dosage; avoid or minimize concomitant use of CNS depressants and other substances associated with abuse, misuse, and addiction (e.g., opioid analgesics, stimulants); and advise patients on the proper disposal of unused drug. If a substance use disorder is suspected, evaluate the patient and institute (or refer them for) early treatment, as appropriate.

5.3 Dependence and Withdrawal Reactions

To reduce the risk of withdrawal reactions, use a gradual taper to discontinue Halcion or reduce the dosage (a patient-specific plan should be used to taper the dose) [see Dosage and Administration (2.3)].

Patients at an increased risk of withdrawal adverse reactions after benzodiazepine discontinuation or rapid dosage reduction include those who take higher dosages, and those who have had longer durations of use.

Acute Withdrawal Reactions

The continued use of benzodiazepines, including Halcion, may lead to clinically significant physical dependence. Abrupt discontinuation or rapid dosage reduction of Halcion after continued use, or administration of flumazenil (a benzodiazepine antagonist) may precipitate acute withdrawal reactions, which can be life-threatening (e.g., seizures) [see Drug Abuse and Dependence (9.3)].

Protracted Withdrawal Syndrome

In some cases, benzodiazepine users have developed a protracted withdrawal syndrome with withdrawal symptoms lasting weeks to more than 12 months [see Drug Abuse and Dependence (9.3)].

5.4 Persistent or Worsening Insomnia

Since sleep disturbances may be the presenting manifestation of a physical and/or psychiatric disorder, symptomatic treatment of insomnia should be initiated only after a careful evaluation of the patient. The failure of insomnia to remit after 7 to 10 days of treatment may indicate the presence of a primary psychiatric and/or medical illness that should be evaluated. Worsening of insomnia or the emergence of new thinking or behavior abnormalities may be the consequence of an unrecognized psychiatric or physical disorder. Such findings have emerged during the course of treatment with sedative-hypnotic drugs.

5.5 "Sleep-driving" and Other Complex Behaviors

Complex behaviors such as "sleep-driving" (i.e., driving while not fully awake after ingestion of a sedative-hypnotic, with amnesia for the event) have been reported with Halcion use. These events can occur in sedative-hypnotic-naïve as well as in sedative-hypnotic-experienced persons. Although behaviors such as sleep-driving may occur with sedative-hypnotics alone at recommended dosages, the use of alcohol and other central nervous system (CNS) depressants with sedative-hypnotics appears to increase the risk of such behaviors, as does the use of sedative-hypnotics at doses exceeding the maximum recommended dose. Due to the risk to the patient and the community, discontinuation of sedative-hypnotics should be strongly considered for patients who report a "sleep-driving" episode.

Other complex behaviors (e.g., preparing and eating food, making phone calls, or having sex) have been reported in patients who are not fully awake after taking a sedative-hypnotic, including Halcion. As with sleep-driving, patients usually do not remember these events.

5.6 Central Nervous System Manifestations

An increase in daytime anxiety has been reported for Halcion after as few as 10 days of continuous use. In some patients this may be a manifestation of interdose withdrawal. If increased daytime anxiety is observed during treatment, discontinuation of treatment may be advisable.

A variety of abnormal thinking and behavior changes have been reported to occur in association with the use of benzodiazepine hypnotics including Halcion. Some of these changes may be characterized by decreased inhibition, e.g., aggressiveness and extroversion that seem excessive, similar to that seen with alcohol and other CNS depressants (e.g., sedative/hypnotics). Other kinds of behavioral changes have also been reported, for example, bizarre behavior, agitation, hallucinations, depersonalization. In primarily depressed patients, the worsening of depression, including suicidal thinking, has been reported in association with the use of benzodiazepines [see Warnings and Precautions (5.9)].

Some adverse reactions reported in association with the use of Halcion such as drowsiness, dizziness, light-headedness, and amnesia appear to be dose related. More serious behavioral phenomena such as confusion, bizarre or abnormal behavior, agitation, and hallucinations may also be dose related, but this evidence is inconclusive. Therapy should be initiated at the lowest effective dose [see Dosage and Administration (2.1)].

It can rarely be determined with certainty whether a particular instance of the abnormal behaviors listed above is drug induced, spontaneous in origin, or a result of an underlying psychiatric or physical disorder. Nonetheless, the emergence of any new behavioral sign or symptom of concern requires careful and immediate evaluation.

Anterograde amnesia of varying severity and paradoxical reactions have been reported following recommended dosages of Halcion. Data from several sources suggest that anterograde amnesia may occur at a higher rate with Halcion than with other benzodiazepine hypnotics. Because HALCION can cause drowsiness and a decreased level of consciousness, patients, particularly the elderly, are at higher risk of falls.

Cases of "traveler's amnesia" have been reported by individuals who have taken Halcion to induce sleep while traveling, such as during an airplane flight. In some of these cases, insufficient time was allowed for the sleep period prior to awakening and before beginning activity. Also, the concomitant use of alcohol may have been a factor in some cases.

5.7 Effects on Driving and Operating Heavy Machinery

Due to its depressant CNS effects, patients receiving Halcion should be cautioned against engaging in hazardous occupations requiring complete mental alertness such as operating machinery or driving a motor vehicle. For the same reason, patients should be cautioned about the concomitant use of alcohol and other CNS depressant drugs during treatment with Halcion.

5.8 Triazolam Interaction With Drugs That Inhibit Metabolism via Cytochrome P450 3A

The initial step in triazolam metabolism is hydroxylation catalyzed by CYP 3A. Drugs that inhibit this metabolic pathway may have a profound effect on the clearance of triazolam.

Strong CYP 3A Inhibitors

Halcion is contraindicated in patients receiving strong inhibitors of CYP 3A such as ketoconazole, itraconazole, nefazodone, ritonavir, indinavir, nelfinavir, saquinavir, and lopinavir [see Contraindications (4), Drug Interactions (7.1)].

Moderate and Weak CYP 3A Inhibitors

Halcion should be used with caution in patients receiving moderate or weak inhibitors of CYP 3A. If coadministered, consider dose reduction of Halcion.

Macrolide Antibiotics

Coadministration of erythromycin increased the maximum plasma concentration, decreased clearance and increased half-life of triazolam [see Drug Interactions (7.1), Clinical Pharmacology (12.3)]; caution and consideration of appropriate triazolam dose reduction are recommended. Similar caution should be observed during coadministration with clarithromycin and other macrolide antibiotics.

Cimetidine

Coadministration of cimetidine increased the maximum plasma concentration, decreased clearance and increased half-life of triazolam [see Drug Interactions (7.1), Clinical Pharmacology (12.3)]; caution and consideration of appropriate triazolam dose reduction are recommended.

5.9 Patients With Depression

Benzodiazepines may worsen depression. Consequently, appropriate precautions (e.g., limiting the total prescription size and increased monitoring for suicidal ideation) should be considered in patients with depression.

5.10 Neonatal Sedation and Withdrawal Syndrome

Use of Halcion late in pregnancy can result in sedation (respiratory depression, lethargy, hypotonia) and/or withdrawal symptoms (hyperreflexia, irritability, restlessness, tremors, inconsolable crying, and feeding difficulties) in the neonate [see Use in Specific Populations (8.1)]. Monitor neonates exposed to HALCION during pregnancy or labor for signs of sedation and monitor neonates exposed to HALCION during pregnancy for signs of withdrawal; manage these neonates accordingly.

5.11 Compromised Respiratory Function

In patients with compromised respiratory function, respiratory depression and apnea have been reported. Closely monitor patients with compromised respiratory function. If signs and symptoms of respiratory depression or apnea occur, consider discontinuation.

6 ADVERSE REACTIONS

The following serious adverse reactions are discussed in greater detail in other sections:

- Risks from Concomitant Use with Opioids [see Warnings and Precautions (5.1)]
- Abuse, Misuse, and Addiction [see Warnings and Precautions (5.2)]
- Dependence and Withdrawal Reactions [see Warnings and Precautions (5.3)]
- Persistent or Worsening Insomnia [see Warnings and Precautions (5.4)]
- "Sleep-driving" and Other Complex Behaviors [see Warnings and Precautions (5.5)]
- Central Nervous System Manifestations [see Warnings and Precautions (5.6)]
- Effects on Driving and Operating Heavy Machinery [see Warnings and Precautions (5.7)]
- Patients with Depression [see Warnings and Precautions (5.9)]
- Neonatal Sedation and Withdrawal Syndrome [see Warnings and Precautions (5.10)]
- Compromised Respiratory Function [see Warnings and Precautions (5.11)]

6.1 Clinical Trials Experience

Because clinical trials are conducted under widely varying conditions, adverse reaction rates observed in the clinical trials of a drug cannot be directly compared to rates in the clinical trials of another drug and may not reflect the rates observed in practice.

The incidences cited below are estimates of clinical reactions among 1003 subjects who participated in the short term (duration of 1 to 42 days) placebo-controlled clinical trials of Halcion.

Adverse reactions leading to discontinuation in two multi-dose placebo controlled clinical trials include coordination disorders, drowsiness, grogginess, somnolence, depression, restlessness, dizziness, lightheadedness, headache, nausea, visual disturbance, nervousness, abdominal distress, bladder trouble, aching limbs, backache, and blepharitis.

Table 1: Common Adverse Drug Reactions in 1% or More of Halcion-Treated Subjects (and Greater than Placebo) Reported in Placebo-Controlled Clinical Trials
Event | Halcion (N=1003) % Patients Reporting | Placebo (N=997) % Patients Reporting
Central Nervous System
Drowsiness | 14.0 | 6.4
Headache | 9.7 | 8.4
Dizziness | 7.8 | 3.1
Nervousness | 5.2 | 4.5
Light-headedness | 4.9 | 0.9
Coordination disorders/ataxia | 4.6 | 0.8
Gastrointestinal
Nausea/vomiting | 4.6 | 3.7

In addition to the common reactions enumerated above in Table1, the following adverse reactions have been reported at an incidence of 0.9% to 0.5%: euphoria, tachycardia, tiredness, confusional states/memory impairment, cramps/pain, depression, and visual disturbances.

Adverse reactions reported at an incidence less than 0.5% include: constipation, taste alterations, diarrhea, dry mouth, dermatitis/allergy, dreaming/nightmares, insomnia, paresthesia, tinnitus, dysesthesia, weakness, congestion, and death from hepatic failure in a patient also receiving diuretic drugs.

6.2 Postmarketing Experience

The following adverse reactions have been identified during post-approval use of Halcion. Because these reactions are reported voluntarily from a population of uncertain size, it is not always possible to reliably estimate their frequency or establish a causal relationship to drug exposure.

General disorders and administration site conditions: Paradoxical drug reaction, chest pain and fatigue
Gastrointestinal disorders: Tongue discomfort, glossitis, stomatitis
Hepatobiliary disorders: Jaundice
Injury, poisoning and procedural complications: Fall
Metabolism and nutrition disorders: Anorexia
Nervous system disorders: Anterograde amnesia, altered state of consciousness, dystonia, sedation, syncope, dysarthria and muscle spasticity
Psychiatric disorders: Confusional state (disorientation, derealisation, depersonalization), mania, agitation, restlessness, irritability, sleep disorder and libido disorder, hallucination, delusion, aggression, somnambulism, and abnormal behavior
Renal and urinary disorders: Urinary retention and urinary incontinence
Reproductive system and breast disorders: Menstruation irregular
Skin and subcutaneous tissue disorders: Pruritis

7 DRUG INTERACTIONS

7.1 Drugs Having Clinically Important Interactions With Halcion

Table 2 includes clinically significant drug interactions with Halcion [see Clinical Pharmacology (12.3)].

Table 2: Clinically Important Drug Interactions with Halcion
Opioids
Clinical implication | The concomitant use of benzodiazepines and opioids increases the risk of respiratory depression because of actions at different receptor sites in the CNS that control respiration. Benzodiazepines interact at GABAA sites and opioids interact primarily at mu receptors. When benzodiazepines and opioids are combined, the potential for benzodiazepines to significantly worsen opioid-related respiratory depression exists.
Prevention or management | Limit dosage and duration of concomitant use of Halcion and opioids, and monitor patients closely for respiratory depression and sedation [see Warnings and Precautions (5.1)].
CNS Depressants
Clinical implication | Triazolam produces additive CNS depressant effects when co-administered with other CNS depressants.
Prevention or management | Limit dosage and duration of Halcion during concomitant use with CNS depressants.
Strong Inhibitors of CYP 3A
Clinical implication | Concomitant use of Halcion with strong CYP3A inhibitors has a profound effect on the clearance of Halcion, resulting in increased concentrations of triazolam and increased risk of adverse reactions [see Clinical Pharmacology (12.3)].
Prevention or management | Do not administer Halcion with a strong CYP3A4 inhibitor [see Contraindications (4), Warnings and Precautions (5.8)].
Moderate and Weak Inhibitors of CYP 3A
Clinical implication | Concomitant use of Halcion with moderate or weak inhibitors of CYP3A inhibitors may increase the concentrations of Halcion, resulting in increased risk of adverse reactions [see Clinical Pharmacology (12.3)].
Prevention or management | Use with caution and consider appropriate dose reduction of HALCION when coadministered with moderate and weak CYP3A inhibitors [see Warnings and Precautions (5.8)].
Strong Inducers of CYP 3A
Clinical implication | Coadministration of triazolam with strong inducers of CYP3A4 can significantly decrease the plasma concentration of triazolam and may decrease effectiveness of triazolam.
Prevention or management | Caution is recommended during coadministration of Halcion with strong inducers of CYP3A4.
Interactions Based on Experience with Other Benzodiazepines or in vitro Studies with Triazolam
Clinical implication | Available data from clinical studies of benzodiazepines other than triazolam, from in vitro studies with triazolam, or from in vitro studies with benzodiazepines other than triazolam suggest a possible drug interaction with triazolam [see Clinical Pharmacology (12.3)].
Prevention or management | Caution is recommended during coadministration of Halcion with any of these drugs. [see Warnings and Precautions (5.8)].

8 USE IN SPECIFIC POPULATIONS

8.1 Pregnancy

Pregnancy Exposure Registry

There is a pregnancy exposure registry that monitors pregnancy outcomes in women exposed to psychiatric medications, including Halcion, during pregnancy. Healthcare providers are encouraged to register patients by calling the National Pregnancy Registry for Psychiatric Medications at 1-866-961-2388 or visiting online at https://womensmentalhealth.org/pregnancyregistry/

Risk Summary

Neonates born to mothers using benzodiazepines late in pregnancy have been reported to experience symptoms of sedation and/or neonatal withdrawal [see Warnings and Precautions (5.10) and Clinical Considerations]. Available data from published observational studies of pregnant women exposed to benzodiazepines do not report a clear association with benzodiazepines and major birth defects (see Data).

The background risk of major birth defects and miscarriage for the indicated population is unknown. All pregnancies have a background risk of birth defect, loss, or other adverse outcomes. In the U.S. general population, the estimated background risk of major birth defects and miscarriage in clinically recognized pregnancies is 2 to 4% and 15 to 20%, respectively.

Clinical Considerations

Fetal/Neonatal Adverse Reactions

Benzodiazepines cross the placenta and may produce respiratory depression, hypotonia, and sedation in neonates. Monitor neonates exposed to Halcion during pregnancy or labor for signs of sedation, respiratory depression, hypotonia, and feeding problems. Monitor neonates exposed to HALCION during pregnancy for signs of withdrawal. Manage these neonates accordingly [see Warnings and Precautions (5.10)].

Data

Human Data

Published data from observational studies on the use of benzodiazepines during pregnancy do not report a clear association with benzodiazepines and major birth defects. Although early studies reported an increased risk of congenital malformations with diazepam and chlordiazepoxide, there was no consistent pattern noted. In addition, the majority of more recent case-control and cohort studies of benzodiazepine use during pregnancy, which were adjusted for confounding exposures to alcohol, tobacco and other medications, have not confirmed these findings.

Animal Data

Oral administration of triazolam to pregnant rats and rabbits during the period of organogenesis caused skeletal developmental changes (variations and malformations) at maternally toxic doses in rats and at doses in rats and rabbits which are approximately equal to or greater than 200 times the maximum recommended human dose (MRHD) of 0.5 mg/day based on mg/m^2 body surface area. Oral administration of triazolam to male and female rats before mating, and continuing during gestation and lactation did not result in embryotoxicity at doses up to approximately 100 times the MRHD based on mg/m^2 body surface area, but did cause an increase in the number of stillbirths and postnatal pup mortalities at doses greater than or equal to approximately 40 times the MRHD based mg/m^2 body surface area. ^14C-triazolam was administered orally to pregnant mice. Drug-related material appeared uniformly distributed in the fetus with ^14C concentrations approximately the same as in the brain of the mother.

8.2 Lactation

Risk Summary

There are reports of sedation, poor feeding and poor weight gain in infants exposed to benzodiazepines through breast milk. There are no data on the presence of triazolam in human milk or the effects on milk production. Triazolam and its metabolites are present in the milk of lactating rats (see Data). When a drug is present in animal milk, it is likely that the drug will be present in human milk.

The developmental and health benefits of breastfeeding should be considered along with the mother's clinical need for HALCION and any potential adverse effects on the breastfed infant from HALCION or from the underlying maternal condition.

Clinical Considerations

Infants exposed to HALCION through breast milk should be monitored for sedation, poor feeding and poor weight gain. A lactating woman may consider interrupting breastfeeding and pumping and discarding breast milk during treatment and for 28 hours (approximately 5 elimination half-lives) after HALCION administration in order to minimize drug exposure to a breast fed infant.

Data

Both triazolam and triazolam metabolites were detected in milk of rats. Lactating rats were orally administered 0.3 mg/kg ^14C-triazolam; drug and metabolite levels were determined in milk collected at 6 and 24 hours after administration.

8.4 Pediatric Use

Safety and effectiveness of Halcion have not been established in pediatric patients.

8.5 Geriatric Use

Elderly patients exhibit higher plasma triazolam concentrations due to reduced clearance as compared with younger subjects at the same dose. Because elderly patients are especially susceptible to dose related adverse reactions and to minimize oversedation, the smallest effective dose should be used [see Dosage and Administration (2.2), Clinical Pharmacology (12.3)].

9 DRUG ABUSE AND DEPENDENCE

9.1 Controlled Substance

Halcion contains triazolam, a Schedule IV controlled substance.

9.2 Abuse

Halcion is a benzodiazepine and a CNS depressant with a potential for abuse and addiction. Abuse is the intentional, non-therapeutic use of a drug, even once, for its desirable psychological or physiological effects. Misuse is the intentional use, for therapeutic purposes, of a drug by an individual in a way other than prescribed by a health care provider or for whom it was not prescribed. Drug addiction is a cluster of behavioral, cognitive, and physiological phenomena that may include a strong desire to take the drug, difficulties in controlling drug use (e.g., continuing drug use despite harmful consequences, giving a higher priority to drug use than other activities and obligations), and possible tolerance or physical dependence. Even taking benzodiazepines as prescribed may put patients at risk for abuse and misuse of their medication. Abuse and misuse of benzodiazepines may lead to addiction.

Abuse and misuse of benzodiazepines often (but not always) involve the use of doses greater than the maximum recommended dosage and commonly involve concomitant use of other medications, alcohol, and/or illicit substances, which is associated with an increased frequency of serious adverse outcomes, including respiratory depression, overdose, or death. Benzodiazepines are often sought by individuals who abuse drugs and other substances, and by individuals with addictive disorders [see Warnings and Precautions (5.2)].

The following adverse reactions have occurred with benzodiazepine abuse and/or misuse: abdominal pain, amnesia, anorexia, anxiety, aggression, ataxia, blurred vision, confusion, depression, disinhibition, disorientation, dizziness, euphoria, impaired concentration and memory, indigestion, irritability, muscle pain, slurred speech, tremors, and vertigo.

The following severe adverse reactions have occurred with benzodiazepine abuse and/or misuse: delirium, paranoia, suicidal ideation and behavior, seizures, coma, breathing difficulty, and death. Death is more often associated with polysubstance use (especially benzodiazepines with other CNS depressants such as opioids and alcohol).

9.3 Dependence

Physical Dependence

Halcion may produce physical dependence from continued therapy. Physical dependence is a state that develops as a result of physiological adaptation in response to repeated drug use, manifested by withdrawal signs and symptoms after abrupt discontinuation or a significant dose reduction of a drug. Abrupt discontinuation or rapid dosage reduction of benzodiazepines or administration of flumazenil, a benzodiazepine antagonist, may precipitate acute withdrawal reactions, including seizures, which can be life-threatening. Patients at an increased risk of withdrawal adverse reactions after benzodiazepine discontinuation or rapid dosage reduction include those who take higher dosages (i.e., higher and/or more frequent doses) and those who have had longer durations of use [see Warnings and Precautions (5.3)].

To reduce the risk of withdrawal reactions, use a gradual taper to discontinue Halcion or reduce the dosage [see Dosage and Administration (2.3), Warnings and Precautions (5.3)].

Acute Withdrawal Signs and Symptoms

Acute withdrawal signs and symptoms associated with benzodiazepines have included abnormal involuntary movements, anxiety, blurred vision, depersonalization, depression, derealization, dizziness, fatigue, gastrointestinal adverse reactions (e.g., nausea, vomiting, diarrhea, weight loss, decreased appetite), headache, hyperacusis, hypertension, irritability, insomnia, memory impairment, muscle pain and stiffness, panic attacks, photophobia, restlessness, tachycardia, and tremor. More severe acute withdrawal signs and symptoms, including life-threatening reactions, have included catatonia, convulsions, delirium tremens, depression, hallucinations, mania, psychosis, seizures, and suicidality.

Protracted Withdrawal Syndrome

Protracted withdrawal syndrome associated with benzodiazepines is characterized by anxiety, cognitive impairment, depression, insomnia, formication, motor symptoms (e.g., weakness, tremor, muscle twitches), paresthesia, and tinnitus that persists beyond 4 to 6 weeks after initial benzodiazepine withdrawal. Protracted withdrawal symptoms may last weeks to more than 12 months. As a result, there may be difficulty in differentiating withdrawal symptoms from potential re-emergence or continuation of symptoms for which the benzodiazepine was being used.

Tolerance

Tolerance to Halcion may develop from continued therapy. Tolerance is a physiological state characterized by a reduced response to a drug after repeated administration (i.e., a higher dose of a drug is required to produce the same effect that was once obtained at a lower dose). Tolerance to the therapeutic effect of Halcion may develop; however, little tolerance develops to the amnestic reactions and other cognitive impairments caused by benzodiazepines.

10 OVERDOSAGE

Overdosage of benzodiazepines is characterized by central nervous system depression ranging from drowsiness to coma. In mild to moderate cases, symptoms can include drowsiness, confusion, dysarthria, lethargy, hypnotic state, diminished reflexes, ataxia, and hypotonia. Rarely, paradoxical or disinhibitory reactions (including agitation, irritability, impulsivity, violent behavior, confusion, restlessness, excitement, and talkativeness) may occur. In severe overdosage cases, patients may develop respiratory depression and coma. Overdosage of benzodiazepines in combination with other CNS depressants (including alcohol and opioids) may be fatal [see Warnings and Precautions (5.2)]. Markedly abnormal (lowered or elevated) blood pressure, heart rate, or respiratory rate raise the concern that additional drugs and/or alcohol are involved in the overdosage.

In managing benzodiazepine overdosage, employ general supportive measures, including intravenous fluids and airway management. Flumazenil, a specific benzodiazepine receptor antagonist indicated for the complete or partial reversal of the sedative effects of benzodiazepines in the management of benzodiazepine overdosage, can lead to withdrawal and adverse reactions, including seizures, particularly in the context of mixed overdosage with drugs that increase seizure risk (e.g., tricyclic and tetracyclic antidepressants) and in patients with long-term benzodiazepine use and physical dependency. The risk of withdrawal seizures with flumazenil use may be increased in patients with epilepsy. Flumazenil is contraindicated in patients who have received a benzodiazepine for control of a potentially life-threatening condition (e.g., status epilepticus). If the decision is made to use flumazenil, it should be used as an adjunct to, not as a substitute for, supportive management of benzodiazepine overdosage. See the flumazenil injection Prescribing Information.

Consider contacting the Poison Help line at (1-800-222-1222) or a medical toxicologist for additional overdosage management recommendations.

11 DESCRIPTION

Halcion Tablets contains triazolam, a triazolobenzodiazepine.

Triazolam is a white crystalline powder, soluble in alcohol and poorly soluble in water. It has a molecular weight of 343.21.

The chemical name for triazolam is 8-chloro-6-(o-chlorophenyl)-1-methyl-4H-s-triazolo-[4,3-α] [1,4] benzodiazepine.

The structural formula is represented below:

Each Halcion tablet, for oral administration, contains 0.25 mg of triazolam.

Inactive ingredients: cellulose, corn starch, docusate sodium, FD&C Blue No. 2, lactose, magnesium stearate, silicon dioxide, sodium benzoate.

12 CLINICAL PHARMACOLOGY

12.1 Mechanism of Action

Triazolam is a benzodiazepine. Triazolam exerts its effect for the short-term treatment of insomnia through binding to the benzodiazepine site of the gamma-aminobutyric acid-A (GABAA) receptors in the brain and enhances GABA-mediated synaptic inhibition.

12.3 Pharmacokinetics

Absorption

Peak plasma levels of triazolam are reached within 2 hours following oral administration. Following recommended doses of Halcion, triazolam peak plasma levels in the range of 1 to 6 ng/mL are seen. The plasma levels achieved are proportional to the dose given. In normal subjects treated for 7 days with four times the recommended dosage, there was no evidence of altered systemic bioavailability, rate of elimination, or accumulation.

Distribution

Extremely high concentrations of triazolam do not displace bilirubin bound to human serum albumin in vitro.

Elimination

Triazolam has a mean plasma elimination half-life in the range of 1.5 to 5.5 hours.

Metabolism

The initial step in triazolam metabolism is cytochrome P450 3A (CYP 3A)-mediated hydroxylation to form 1-hydroxytriazolam and 4-hydroxytriazolam, which are subsequently conjugated to form glucuronides.

Excretion

Triazolam and its metabolites, principally as conjugated glucuronides which are presumably inactive, are excreted primarily in the urine. Only small amounts of unmetabolized triazolam appear in the urine. The two primary metabolites accounted for 79.9% of urinary excretion. Urinary excretion appeared to be biphasic in its time course.

Specific Populations

Geriatric Patients

In a study of elderly (62 to 83 years old) versus younger subjects (21 to 41 years old) who received triazolam at the same dose levels (0.125 mg and 0.25 mg), the elderly experienced both greater sedation and impairment of psychomotor performance. These effects resulted largely from higher plasma concentrations of triazolam in the elderly.

Drug Interaction Studies

The effect of other drugs on triazolam:

Macrolide Antibiotics

Coadministration of erythromycin increased the maximum plasma concentration of triazolam by 46%, decreased clearance by 53%, and increased half-life by 35%.

Cimetidine

Coadministration of cimetidine increased the maximum plasma concentration of triazolam by 51%, decreased clearance by 55%, and increased half-life by 68%.

Isoniazid

Coadministration of isoniazid increased the maximum plasma concentration of triazolam by 20%, decreased clearance by 42%, and increased half-life by 31%.

Oral Contraceptives

Coadministration of oral contraceptives increased maximum plasma concentration by 6%, decreased clearance by 32%, and increased half-life by 16%.

Grapefruit Juice

Coadministration of grapefruit juice increased the maximum plasma concentration of triazolam by 25%, increased the area under the concentration curve by 48%, and increased half-life by 18%.

Ranitidine

Coadministration of ranitidine increased the maximum plasma concentration of triazolam by 30%, increased the area under the concentration curve by 27%, and increased half-life by 3.3%. Caution is recommended during coadministration with triazolam. Available data from clinical studies of benzodiazepines other than triazolam suggest a possible drug interaction with triazolam for the following: fluvoxamine, diltiazem, and verapamil. Data from in vitro studies of triazolam suggest a possible drug interaction with triazolam for the following: sertraline and paroxetine. Data from in vitro studies of benzodiazepines other than triazolam suggest a possible drug interaction with triazolam for the following: ergotamine, cyclosporine, amiodarone, nicardipine, and nifedipine.

The effect of triazolam on other drugs:

Warfarin

Halcion Tablets 0.5 mg, in two separate studies, did not affect the prothrombin times or plasma warfarin levels in male volunteers administered sodium warfarin orally.

13 NONCLINICAL TOXICOLOGY

13.1 Carcinogenesis, Mutagenesis, Impairment of Fertility

Carcinogenesis

No evidence of carcinogenic potential was observed in rats or mice administered triazolam in the diet for 24-months at doses greater than or equal to 900 times the MRHD of 0.5 mg, based on mg/m^2 body surface area.

Mutagenesis

Triazolam was not mutagenic in the in vitro Ames bacterial reverse mutation assay, and no DNA damage was observed in an in vitro alkaline elution assay in Chinese hamster lung fibroblast cells.

Impairment of Fertility

Female rats were administered triazolam in the diet for 14 days before cohabitation, during gestation, and until 21 days post parturition, and male rats for 60 days before cohabitation. No effects on mating or fertility were observed in rats up to 5 mg/kg/day which is approximately 100 times the MRHD of 0.5 mg/day, based on mg/m^2 body surface area.

16 HOW SUPPLIED/STORAGE AND HANDLING

Halcion is supplied as a powder blue, elliptical, scored tablet in the following strengths and package configurations:

Package Configuration | Tablet Strength (mg) | NDC | Print
Reverse numbered Unit Dose (100) | 0.25 mg | NDC 0009-0017-55 | HALCION 0.25
Bottles of 10 | 0.25 mg | NDC 0009-0017-58 | HALCION 0.25

STORAGE AND HANDLING

Store at controlled room temperature 20° to 25°C (68° to 77°F) [see USP Controlled Room Temperature].

17 PATIENT COUNSELING INFORMATION

Advise the patient to read the FDA-approved patient labeling (Medication Guide).

Risks from Concomitant Use with Opioids

Advise both patients and caregivers about the risks of potentially fatal respiratory depression and sedation when Halcion is used with opioids and not to use such drugs concomitantly unless supervised by a healthcare provider. Advise patients not to drive or operate heavy machinery until the effects of concomitant use with the opioid have been determined [see Warnings and Precautions (5.1), Drug Interactions (7.1)].

Abuse, Misuse, and Addiction

Inform patients that the use of Halcion, even at recommended dosages, exposes users to risks of abuse, misuse, and addiction, which can lead to overdose and death, especially when used in combination with other medications (e.g., opioid analgesics), alcohol, and/or illicit substances. Inform patients about the signs and symptoms of benzodiazepine abuse, misuse, and addiction; to seek medical help if they develop these signs and/or symptoms; and on the proper disposal of unused drug [see Warnings and Precautions (5.2), Drug Abuse and Dependence (9.2)].

Withdrawal Reactions

Inform patients that the continued use of Halcion may lead to clinically significant physical dependence and that abrupt discontinuation or rapid dosage reduction of Halcion may precipitate acute withdrawal reactions, which can be life-threatening. Inform patients that in some cases, patients taking benzodiazepines have developed a protracted withdrawal syndrome with withdrawal symptoms lasting weeks to more than 12 months. Instruct patients that discontinuation or dosage reduction of Halcion may require a slow taper [see Warnings and Precautions (5.3), Drug Abuse and Dependence (9.3)].

"Sleep-driving" and Other Complex Behaviors

There have been reports of people getting out of bed after taking a sedative-hypnotic and driving their cars while not fully awake, often with no memory of the event. Advise patients to report similar experiences to their healthcare provider immediately, since "sleep-driving" can be dangerous. This behavior is more likely to occur when sedative-hypnotics are taken with alcohol or other CNS depressants [see Warnings and Precautions (5.5)]. Other complex behaviors (e.g., preparing and eating food, making phone calls, or having sex) have been reported in patients who are not fully awake after taking a sedative hypnotic. As with sleep-driving, patients usually do not remember these events.

Advise patients that increased drowsiness and decreased consciousness may increase the risk of falls in some patients.

Effects on Driving and Operating Heavy Machinery

Caution patients against driving a motor vehicle or operating heavy machinery until the effects of taking Halcion are determined due to its CNS depressant effects. Also advise patients to avoid the use of alcohol or other CNS depressants while taking Halcion [see Warnings and Precautions (5.7)].

Patients with Depression

Advise patients, their families and caregivers to look out for any signs of suicidality or worsening depression, and to inform the patient's prescriber or healthcare provider immediately [see Warnings and Precautions (5.9)].

Concomitant Medications

Advise patients to inform their healthcare provider of all medicines they take, including prescription and nonprescription medicines, vitamins and herbal supplements [see Drug Interactions (7.1)].

Grapefruit Juice

Advise patients to avoid eating grapefruit or drinking grapefruit juice while taking Halcion [see Drug Interactions (7.1)].

Pregnancy

Advise pregnant females that use of HALCION late in pregnancy can result in sedation (respiratory depression, lethargy, hypotonia) and/or withdrawal symptoms (hyperreflexia, irritability, restlessness, tremors, inconsolable crying, and feeding difficulties) in newborns [see Warnings and Precautions (5.10), Use in Specific Populations (8.1)]. Instruct patients to inform their healthcare provider if they are pregnant.

Advise patients that there is a pregnancy exposure registry that monitors pregnancy outcomes in women exposed to HALCION during pregnancy [see Use in Specific Populations (8.1)].

Lactation

Instruct patients to notify their healthcare provider if they are breastfeeding or intend to breastfeed. Instruct breastfeeding patients using HALCION to monitor infants for excessive sedation, poor feeding and poor weight gain, and to seek medical attention if they notice these signs. A lactating woman may consider pumping and discarding breastmilk during treatment and for 28 hours after Halcion administration to minimize drug exposure to a breastfed infant [see Use in Specific Populations (8.2)].

This product's labeling may have been updated. For the most recent prescribing information, please visit www.pfizer.com.

LAB-0666-14.0

MEDICATION GUIDE
HALCION (HAL-cee-on)
(triazolam)
tablets, CIV

What is the most important information I should know about HALCION?

- HALCION is a benzodiazepine medicine. Taking benzodiazepines with opioid medicines, alcohol, or other central nervous system (CNS) depressants (including street drugs) can cause severe drowsiness, breathing problems (respiratory depression), coma and death. Get emergency help right away if any of the following happens:
  - shallow or slowed breathing
  - breathing stops (which may lead to the heart stopping)
  - excessive sleepiness (sedation)
Do not drive or operate heavy machinery until you know how taking HALCION with opioids affects you.
- Risk of abuse, misuse, and addiction. There is a risk of abuse, misuse, and addiction with benzodiazepines, including HALCION which can lead to overdose and serious side effects including coma and death.
  - Serious side effects including coma and death have happened in people who have abused or misused benzodiazepines, including HALCION. These serious side effects may also include delirium, paranoia, suicidal thoughts or actions, seizures, and difficulty breathing. Call your healthcare provider or go to the nearest hospital emergency room right away if you get any of these serious side effects.
  - You can develop an addiction even if you take HALCION as prescribed by your healthcare provider.
  - Take HALCION exactly as your healthcare provider prescribed.
  - Do not share your HALCION with other people.
  - Keep HALCION in a safe place and away from children.
- Physical dependence and withdrawal reactions. HALCION can cause physical dependence and withdrawal reactions.
  - Do not suddenly stop taking HALCION. Stopping HALCION suddenly can cause serious and life-threatening side effects, including unusual movements, responses, or expressions, seizures, sudden and severe mental or nervous system changes, depression, seeing or hearing things that others do not see or hear, an extreme increase in activity or talking, losing touch with reality, and suicidal thoughts or actions. Call your healthcare provider or go to the nearest hospital emergency room right away if you get any of these symptoms.
  - Some people who suddenly stop benzodiazepines, have symptoms that can last for several weeks to more than 12 months, including, anxiety, trouble remembering, learning, or concentrating, depression, problems sleeping feeling like insects are crawling under your skin, weakness, shaking, muscle twitching, burning or prickling feeling in your hands, arms, legs or feet, and ringing in your ears.
  - Physical dependence is not the same as drug addiction. Your healthcare provider can tell you more about the differences between physical dependence and drug addiction.
  - Do not take more HALCION than prescribed or take HALCION for longer than prescribed.
- After taking HALCION, you may get up out of bed while not being fully awake and do an activity that you do not know you are doing. The next morning, you may not remember that you did anything during the night. You have a higher chance for doing these activities if you drink alcohol or take other medicines that make you sleepy with HALCION. Reported activities include:

- driving a car ("sleep-driving")
- making and eating food
- talking on the phone

- having sex
- sleep-walking

Call your healthcare provider right away if you find out that you have done any of the above activities after taking HALCION.

What is HALCION?

HALCION is a prescription medicine used in adults for the short-term treatment of a sleep problem called insomnia. HALCION is usually taken for 7 to 10 days.

- HALCION is a federal controlled substance (CIV) because it contains triazolam that can be abused or lead to dependence. Keep HALCION in a safe place to prevent misuse and abuse. Selling or giving away HALCION may harm others, and is against the law. Tell your healthcare provider if you have abused or been dependent on alcohol, prescription medicines or street drugs.
- It is not known if HALCION is safe and effective in children.
- It is not known if HALCION is safe and effective for use longer than 2 to 3 weeks.

Do not take HALCION if you:

- are allergic to triazolam, other benzodiazepines, or any of the ingredients in HALCION. Severe allergic reactions including swelling of the tongue or throat, trouble breathing and throat closing have happened and may lead to death. Get medical help right away if you have an allergic reaction to HALCION. See the end of this Medication Guide for a complete list of ingredients in HALCION.
- take antifungal medicines including ketoconazole and itraconazole
- take a medicine to treat depression called nefazodone
- take medicines to treat human immunodeficiency virus (HIV)-1 infection called protease inhibitors.

Before you take HALCION, tell your healthcare provider about all of your medical conditions, including if you:

- have a history of depression, mood problems, mental illness, suicidal thoughts or behavior
- have a history of drug or alcohol abuse or addiction
- have lung problems, breathing problems, or sleep apnea
- are pregnant or plan to become pregnant.
  - Taking HALCION late in pregnancy may cause your baby to have symptoms of sedation (breathing problems, sluggishness, low muscle tone), and/or withdrawal symptoms (jitteriness, irritability, restlessness, shaking, excessive crying, feeding problems).
  - Tell your healthcare provider right away if you become pregnant or think you are pregnant during treatment with HALCION.
  - There is a pregnancy registry for women who take HALCION during pregnancy. The purpose of the registry is to collect information about the health of you and your baby. If you become pregnant during treatment with HALCION, talk to your healthcare provider about registering with the National Pregnancy Registry for Psychiatric Medications. You can register by calling 1-866-961-2388 or visiting https://womensmentalhealth.org/pregnancyregistry/
- are breastfeeding or plan to breastfeed. It is not known if HALCION can pass through your breast milk.
  - Breastfeeding during treatment with HALCION may cause your baby to have sleepiness, feeding problems, and decreased weight gain.
  - Talk to your healthcare provider about the best way to feed your baby if you take HALCION.

Tell your healthcare provider about all of the medicines you take, including prescription and over-the-counter medicines, vitamins, and herbal supplements.

Taking HALCION with certain other medicines can cause side effects or affect how well HALCION or the other medicines work. Do not start or stop other medicines without talking to your healthcare provider.

How should I take HALCION?

- Take HALCION exactly as your healthcare provider tells you to take it.
- Take HALCION right before you get into bed.
- Do not eat grapefruit or drink grapefruit juice during treatment with HALCION.
- Call your healthcare provider if your insomnia worsens or is not better within 7 to 10 days of treatment with HALCION. This may mean that there is another condition causing your sleep problem.
- If you take too much HALCION, call your healthcare provider or have somebody drive you to the nearest hospital emergency room right away.

What are the possible side effects of HALCION?

HALCION may cause serious side effects, including:

- See "What is the most important information I should know about HALCION?"
- Increased daytime anxiety.
- Abnormal thoughts and behavior. Symptoms include more outgoing or aggressive behavior than normal, confusion, agitation, hallucinations, worsening of depression, and suicidal thoughts or actions.
- Memory loss
- HALCION can make you sleepy or dizzy and can slow your thinking and motor skills.
  - Do not drive, operate heavy machinery, or do other dangerous activities until you know how HALCION affects you.
  - Do not drink alcohol or take other drugs that may make you sleepy or dizzy while taking HALCION without first talking to your healthcare provider. When taken with alcohol or drugs that cause sleepiness or dizziness, HALCION may make your sleepiness or dizziness much worse.
- Worsening depression. Call your healthcare provider right away if you have any thoughts of suicide or dying or worsening depression.

The most common side effects of HALCION include:

- drowsiness
- dizziness

- light-headedness
- difficulty with coordination

Elderly people have an increased risk of dose related side effects during treatment with HALCION.

These are not all the possible side effects of HALCION.

Call your doctor for medical advice about side effects. You may report side effects to FDA at 1-800-FDA-1088.

How should I store HALCION?

- Store HALCION at room temperature between 68°F to 77° F (20°C to 25°C).
- Keep HALCION and all medicines out of the reach of children

General information about the safe and effective use of HALCION.

Medicines are sometimes prescribed for purposes other than those listed in a Medication Guide. Do not use HALCION for a condition for which it was not prescribed. Do not give HALCION to other people, even if they have the same symptoms that you have. It may harm them. You can ask your healthcare provider or pharmacist for information about HALCION that is written for healthcare professionals.

What are the ingredients in HALCION?

Active ingredient: triazolam

Inactive ingredients: cellulose, corn starch, docusate sodium, FD&C Blue No. 2, lactose, magnesium stearate, silicon dioxide, sodium benzoate.

If you would like more information, call 1-800-438-1985 or visit www.pfizer.com.

LAB-0259-19.0

This Medication Guide has been approved by the U.S. Food and Drug Administration. Revised 7/2024

PRINCIPAL DISPLAY PANEL - 0.25 mg Tablet Blister Pack

Halcion®
triazolam tablets, USP
CIV
0.25 mg
Pharmacia & Upjohn Co LLC
A sub. of Pfizer Inc.
NY, NY 10001
75106078

EXP &
LOT AREA

PRINCIPAL DISPLAY PANEL - 0.25 mg Tablet Blister Pack Carton

ALWAYS DISPENSE WITH MEDICATION GUIDE

NDC 0009-0017-55

Pfizer

Halcion®
triazolam tablets,
USP
CIV

0.25 mg

For in-institution use only

100 Tablets
Reverse Numbered
Rx only

PRINCIPAL DISPLAY PANEL - 0.25 mg Tablet Bottle Label

ALWAYS DISPENSE WITH MEDICATION GUIDE

NDC 0009-0017-58

Pfizer

Halcion®
triazolam
tablets, USP
CIV

0.25 mg

10 Tablets
Rx only